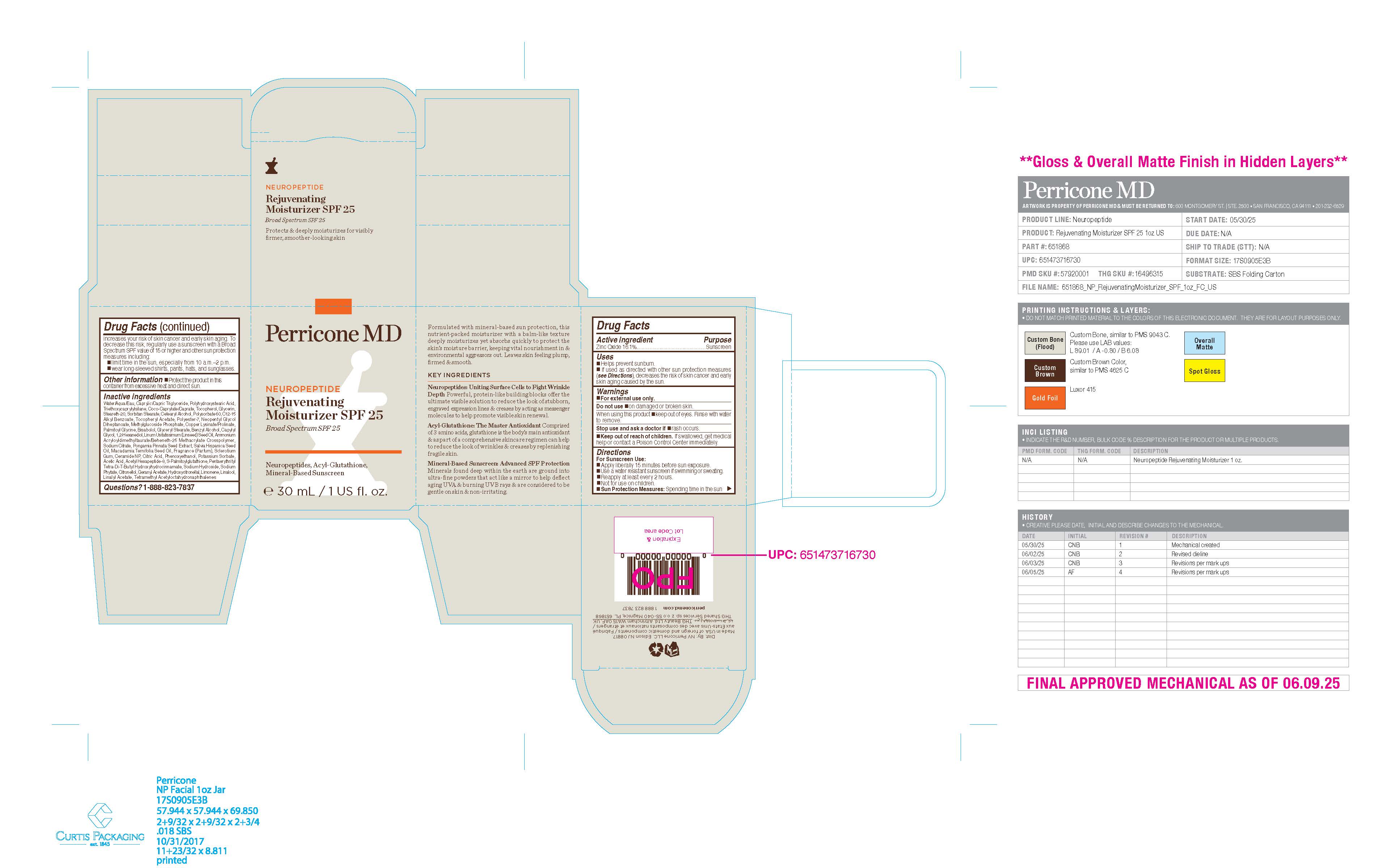 DRUG LABEL: Perricone MD NEUROPEPTIDE Rejuvenating Moisturizer SPF 25 Broad Spectrum SPF 25
NDC: 84448-232 | Form: CREAM
Manufacturer: THG Beauty USA LLC
Category: otc | Type: HUMAN OTC DRUG LABEL
Date: 20251219

ACTIVE INGREDIENTS: ZINC OXIDE 16.1 g/100 mL
INACTIVE INGREDIENTS: CITRIC ACID; GERANYL ACETATE; MACADAMIA TERNIFOLIA SEED OIL; ALPHA-TOCOPHEROL ACETATE; POLYESTER-7; SODIUM PHYTATE; CAPRYLIC/CAPRIC TRIGLYCERIDE; PALMITOYL GLYCINE; GLYCERYL STEARATE; STEARETH-20; CETEARYL ALCOHOL; SODIUM CITRATE; PHENOXYETHANOL; SODIUM HYDROXIDE; ACETYL HEXAPEPTIDE-8; CAPRYLYL GLYCOL; GLUTATHIONE PALMITAMIDE; TETRAMETHYL ACETYLOCTAHYDRONAPHTHALENES; TRIETHOXYCAPRYLYLSILANE; COCO-CAPRYLATE/CAPRATE; TOCOPHEROL; NEOPENTYL GLYCOL DIHEPTANOATE; SCLEROTIUM GUM; CERAMIDE NP; PENTAERYTHRITYL TETRA-DI-T-BUTYL HYDROXYHYDROCINNAMATE; SORBITAN STEARATE; POTASSIUM SORBATE; ACETIC ACID; GLYCERIN; COPPER LYSINATE; HYDROXYCITRONELLAL; LIMONENE, (+/-)-; WATER; POLYHYDROXYSTEARIC ACID (2300 MW); FRAGRANCE 13576; 1,2-HEXANEDIOL; LINUM USITATISSIMUM (LINSEED) SEED OIL; AMMONIUM ACRYLOYLDIMETHYLTAURATE/BEHENETH-25 METHACRYLATE CROSSPOLYMER (52000 MPA.S); SALVIA HISPANICA SEED OIL; CITRONELLOL; LINALOOL; LINALYL ACETATE; BENZYL ALCOHOL; PONGAMIA PINNATA SEED; METHYL-D-GLUCOPYRANOSIDE; POLYSORBATE 60; C12-15 ALKYL BENZOATE; BISABOLOL

ACTIVE INGREDIENT

Zinc Oxide 16.1%

PURPOSE

Sunscreen

Uses
■ Helps prevent sunburn.
■ If used as directed with other sun protection measures (see Directions), decreases the risk of skin cancer and early skin aging caused by the sun

WARNINGS

For external use only.

Do not use ■ on damaged or broken skin.

When using this product ■ keep out of eyes. Rinse with water to remove.

Stop use and ask a doctor if ■ rash occurs.

■ Keep out of reach of children. If swallowed, get medical help or contact a Poison Control Center immediately.

Directions
For Sunscreen Use:
■ Apply liberally 15 minutes before sun exposure.
■ Use a water resistant sunscreen if swimming or sweating.
■ Reapply at least every 2 hours.
■ Not for use on children.
■ Sun Protection Measures: Spending time in the sun increases your risk of skin cancer and early skin aging. To
decrease this risk, regularly use a sunscreen with a Broad Spectrum SPF value of 15 or higher and other sun protection
measures including:
■ limit time in the sun, especially from 10 a.m.–2 p.m.
■ wear long-sleeved shirts, pants, hats, and sunglasses.

OTHER SAFETY INFORMATION

■ Protect the product in this container from excessive heat and direct sun.

INACTIVE INGREDIENT

Water/Aqua/Eau, Caprylic/Capric Triglyceride, Polyhydroxystearic Acid,
Triethoxycaprylylsilane, Coco-Caprylate/Caprate, Tocopherol, Glycerin,
Steareth-20, Sorbitan Stearate, Cetearyl Alcohol, Polysorbate 60, C12-15
Alkyl Benzoate, Tocopheryl Acetate, Polyester-7, Neopentyl Glycol
Diheptanoate, Methylglucoside Phosphate, Copper Lysinate/Prolinate,
Palmitoyl Glycine, Bisabolol, Glyceryl Stearate, Benzyl Alcohol, Capylyl
Glycol, 1,2-Hexanediol, Linum Usitatissimum (Linseed) Seed Oil, Ammonium
Acryloyldimethyltaurate/Beheneth-25 Methacrylate Crosspolymer,
Sodium Citrate, Pongamia Pinnata Seed Extract, Salvia Hispanica Seed
Oil, Macadamia Ternifolia Seed Oil, Fragrance (Parfum), Sclerotium
Gum, Ceramide NP, Citric Acid, Phenoxyethanol, Potassium Sorbate,
Acetic Acid, Acetyl Hexapeptide-8, S-Palmitoylglutathione, Pentaerythrityl
Tetra-Di-T-Butyl Hydroxyhydrocinnamate, Sodium Hydroxide, Sodium
Phytate, Citronellol, Geranyl Acetate, Hydroxycitronellal, Limonene, Linalool,
Linalyl Acetate, Tetramethyl Acetyloctahydronaphthalenes

QUESTIONS

1-888-823-7837